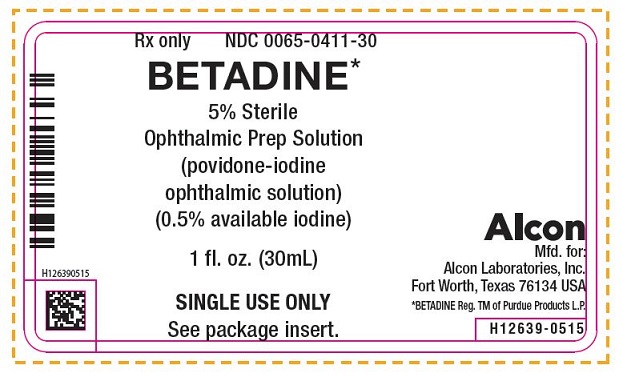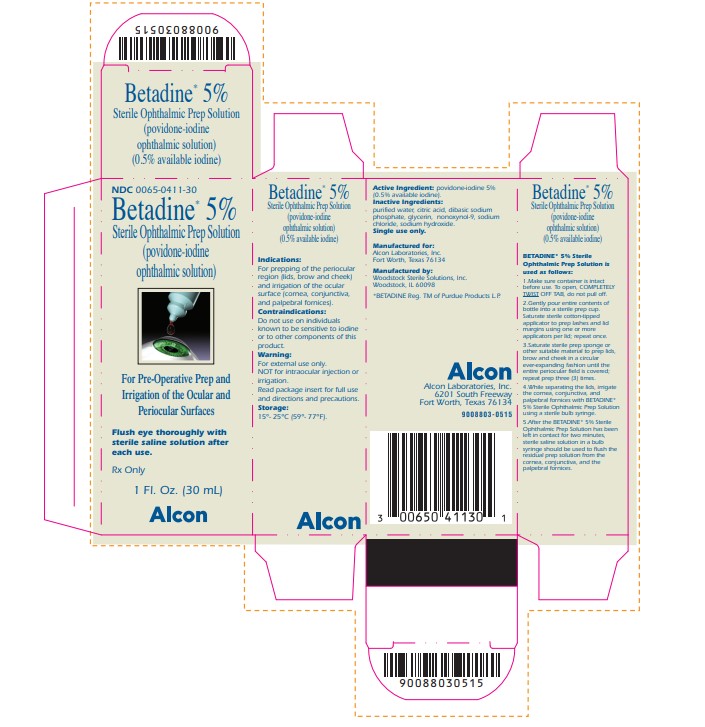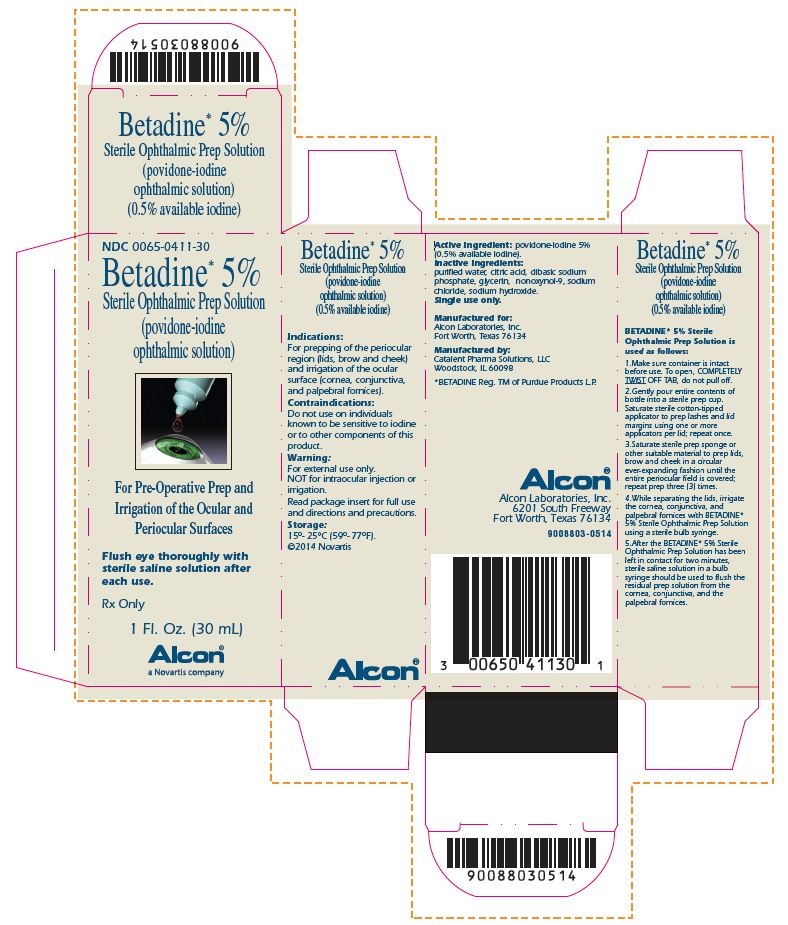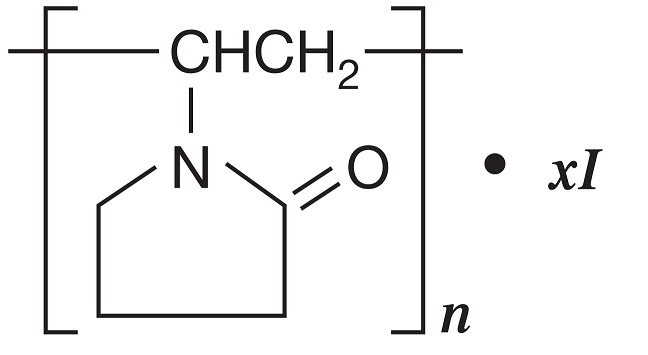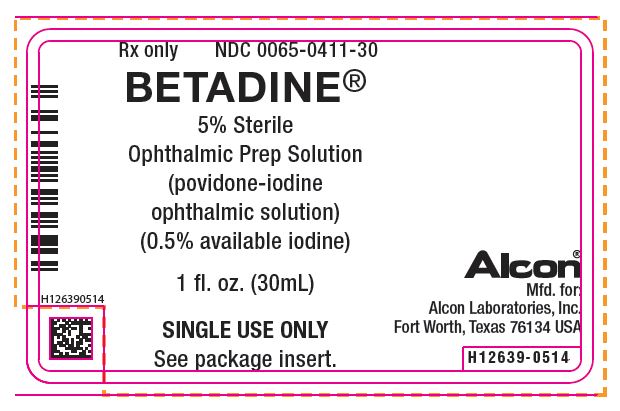 DRUG LABEL: Betadine
NDC: 0065-0411 | Form: SOLUTION
Manufacturer: Alcon Laboratories, Inc.
Category: prescription | Type: HUMAN PRESCRIPTION DRUG LABEL
Date: 20220629

ACTIVE INGREDIENTS: POVIDONE-IODINE 5 mg/1 mL
INACTIVE INGREDIENTS: CITRIC ACID MONOHYDRATE; GLYCERIN; NONOXYNOL-9; SODIUM CHLORIDE; SODIUM HYDROXIDE; SODIUM PHOSPHATE, DIBASIC

BETADINE* 5%
Sterile Ophthalmic
Prep Solution
(povidone-iodine ophthalmic solution)
(0.5% available iodine)

DESCRIPTION

DESCRIPTION: Povidone-Iodine is a broad-spectrum microbicide with the chemical formulas: 2-pyrrolidinone, 1- ethenyl-, homopolymer, compound with iodine; 1-vinyl-2-pyrrolidinone polymer, compound with iodine.
The structural formula is as follows:

BETADINE* 5% Sterile Ophthalmic Prep Solution contains 5% povidone-iodine (0.5% available iodine) as a sterile dark brown solution stabilized by glycerin. Inactive Ingredients: purified water, citric acid, glycerin, nonoxynol-9, sodium chloride, sodium hydroxide, and dibasic sodium phosphate.

CLINICAL PHARMACOLOGY

CLINICAL PHARMACOLOGY: A placebo-controlled study in 38 normal volunteers yielded data for 36 subjects who showed a mean log10 reduction of 3.05 log10 units in total aerobes at 10 minutes following prepping the skin with BETADINE* 5% Sterile Ophthalmic Prep Solution compared with reduction of 1.58 log10 units after prepping with vehicle free of the iodine complex. This placebo-controlled study indicates a mean log10 reduction by the iodine complex compared with the control solution of 1.47 log10 units at 10 minutes and 1.79 log10 units at 45 minutes. The base-line mean aerobic bacterial count was 7,586 organisms/cm2.

INDICATIONS AND USAGE: BETADINE* 5% Sterile Ophthalmic Prep Solution for the eye is indicated for prepping of the periocular region (lids, brow, and cheek) and irrigation of the ocular surface (cornea, conjunctiva, and palpebral fornices).

CONTRAINDICATIONS

CONTRAINDICATIONS: Do not use on individuals known to be sensitive to iodine, or other components of this product.

WARNINGS

WARNINGS: FOR EXTERNAL USE ONLY. NOT FOR INTRAOCULAR INJECTION OR IRRIGATION.

PRECAUTIONS:

GENERAL PRECAUTIONS

General: No studies are available in patients with thyroid disorders; therefore, caution is advised in using BETADINE* 5% Sterile Ophthalmic Prep Solution in these patients due to the possibility of iodine absorption.

CARCINOGENESIS AND MUTAGENESIS AND IMPAIRMENT OF FERTILITY

Carcinogenesis, Mutagenesis, Impairment of Fertility: No long term studies in animals have been performed to evaluate the carcinogenic or mutagenic potential of povidone-iodine. One report of the mutagenic potential of povidone-iodine indicated that it was positive in a modification of the Ames S. typhimurium model, but these results could not be reproduced by another researcher. Another test using mouse lymphoma and Balb/3T3 cells showed that povidone-iodine has no significant mutagenic or transformation capabilities. Other data indicated that it does not produce mutagenic effects in mice or hamsters according to the dominant lethal test, micronucleus test, and chromosome analysis.

PREGNANCY

Pregnancy: Animal reproduction studies have not been conducted with BETADINE* 5% Sterile Ophthalmic Prep Solution. It is also not known whether BETADINE* 5% Sterile Ophthalmic Prep Solution can cause fetal harm when administered to a pregnant woman or can affect reproductive capacity. BETADINE* 5% Sterile Ophthalmic Prep Solution should only be used on a pregnant woman if clearly needed.

NURSING MOTHERS

Nursing Mothers: Because of the potential for serious adverse reactions in nursing infants from BETADINE* 5% Sterile Ophthalmic Prep Solution, a decision should be made to discontinue nursing or discontinue the drug, taking into account the importance of the drug to the mother.

PEDIATRIC USE

Pediatric Use: Safety and effectiveness in pediatric patients have not been established.

GERIATRIC USE

Geriatric Use: No overall differences in safety or effectiveness have been observed between elderly and younger patients.

ADVERSE REACTIONS

ADVERSE REACTIONS: Local sensitivity has been exhibited by some individuals to povidone-iodine ophthalmic solution.

DOSAGE AND ADMINISTRATION: While the inner surface and contents of the immediate container (i.e. bottle) are sterile, the outer surface of the bottle is not sterile. The use of the bottle in a sterile field should be avoided. BETADINE* 5% Sterile Ophthalmic Prep Solution is used as follows:

BETADINE* 5% Sterile Ophthalmic Prep Solution is used as follows:

1. Make sure container is intact before use. To open, COMPLETELY TWIST OFF TAB, do not pull off.
2. Gently pour entire contents of bottle into a sterile prep cup. Saturate sterile cotton-tipped applicator to prep lashes and lid margins using one or more applicators per lid; repeat once.
3. Saturate sterile prep sponge or other suitable material to prep lids, brow and cheek in a circular ever-expanding fashion until the entire field is covered; repeat prep three (3) times.
4. While separating the lids, irrigate the cornea, conjunctiva and palpebral fornices with BETADINE* 5% Sterile Ophthalmic Prep Solution using a sterile bulb syringe.
5. After the BETADINE* 5% Sterile Ophthalmic Prep Solution has been left in contact for two minutes, sterile saline solution in a bulb syringe should be used to flush the residual prep solution from the cornea, conjunctiva, and the palpebral fornices.

HOW SUPPLIED

HOW SUPPLIED: BETADINE* 5% Sterile Ophthalmic Prep Solution is packaged under sterile conditions, and supplied in 1 fl oz (30 mL) form sealed blue HDPE bottles. Twenty-four (24) bottles are packed in each shipper.

NDC 0065-0411-30
Store at 15°C to 25°C (59°F-77°F).
Rx Only
Single-use only

@2021 Alcon Inc.

Alcon
Manufactured for:
Alcon Laboratories, Inc.
6201 South Freeway
Fort Worth, TX 76134

Manufactured by:
Woodstock Sterile Solutions, Inc.
Woodstock, IL 60098

*BETADINE is a registered trademark of Purdue Products L.P.

STW-AC6024-642R01

Principal Display Panel

NDC 0065-0411-30
Betadine* 5%
Sterile Ophthalmic Prep Solution
(povidone-iodine
ophthalmic solution)
For Pre-Operative Prep and
Irrigation of the Ocular and
Periocular Surfaces
Flush eye thoroughly with
sterile saline solution after
each use.
Rx Only
1 Fl. Oz. (30 mL)
Alcon
Indications:
For prepping of the periocular
region (lids, brow, and cheek)
and irrigation of the ocular
surface (cornea, conjunctiva,
and palpebral fornices).
Contraindications:
Do not use on individuals
known to be sensitive to iodine
or other components of this
product.
Warning:
For external use only.
NOT for intraocular injection or
irrigation.
Read package insert for full use
and directions and precautions.
Storage:
15°- 25°C (59°- 77°F).
Active Ingredient: povidone-iodine 5%
(0.5% available iodine).
Inactive Ingredients:
purified water, citric acid, dibasic sodium
phosphate, glycerin, nonoxynol-9, sodium
chloride, sodium hydroxide.
Single use only.
Manufactured for:
Alcon Laboratories, Inc.
Fort Worth, Texas 76134
Manufactured by:
Woodstock Sterile Solutions
Woodstock, IL 60098
*BETADINE Reg. TM of Purdue Products L.P.
Alcon
Alcon Laboratories, Inc.
6201 South Freeway
Fort Worth, Texas 76134
9008803-0515

NDC 0065-0411-30
Betadine* 5%
Sterile Ophthalmic Prep Solution
(povidone-iodine ophthalmic solution)
For Pre-Operative Prep and Irrigation of the Ocular and Periocular Surfaces
Flush eye thoroughly with sterile saline solution after each use.
Rx Only
1 Fl. Oz. (30 mL)
Alcon®
a Novartis company
Indications:
For prepping of the periocular region (lids, brow, and cheek) and irrigation of the ocular surface (cornea, conjunctiva, and palpebral fornices).
Contraindications:
Do not use on individuals known to be sensitive to iodine or other components of this product.
Warning:
For external use only.
NOT for intraocular injection or irrigation.
Read package insert for full use and directions and precautions.
Storage:
15°- 25°C (59°- 77°F).
©2014 Novartis
Active Ingredient: povidone-iodine 5% (0.5% available iodine).
Inactive Ingredients: purified water, citric acid, dibasic sodium phosphate, glycerin, nonoxynol-9, sodium chloride, sodium hydroxide.
Single use only.
Manufactured for:
Alcon Laboratories, Inc.
Fort Worth, Texas 76134
Manufactured by:
Catalent Pharma Solutions, LLC
Woodstock, IL 60098
*BETADINE Reg. TM of Purdue Products L.P.
Alcon®
Alcon Laboratories, Inc.
6201 South Freeway
Fort Worth, Texas 76134
9008803-0514

Rx only NDC 0065-0411-30
Betadine*
5% Sterile
Ophthalmic Prep Solution
(povidone-iodine
ophthalmic solution)
(0.5% available iodine)
1 fl. oz. (30mL)
SINGLE USE ONLY
See package insert.
Alcon
Mfd. for
Alcon Laboratories, Inc.
Fort Worth, Texas 76134 USA
*BETADINE Reg. TM of Purdue Products L.P.
H12639-0515

Rx only NDC 0065-0411-30
Betadine®
5% Sterile
Ophthalmic Prep Solution
(povidone-iodine
ophthalmic solution)
(0.5% available iodine)
1 fl. oz. (30mL)
SINGLE USE ONLY
See package insert.
Alcon
Mfd. for
Alcon Laboratories, Inc.
Fort Worth, Texas 76134 USA
H12639-0514